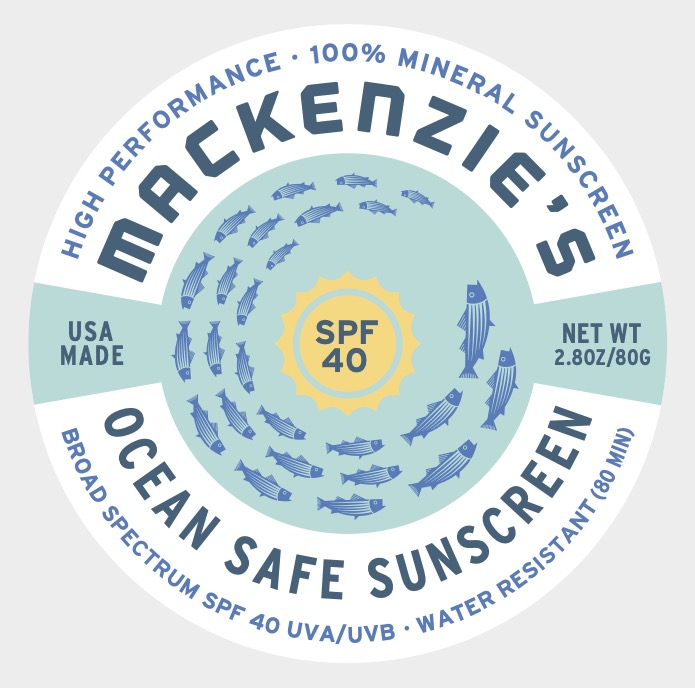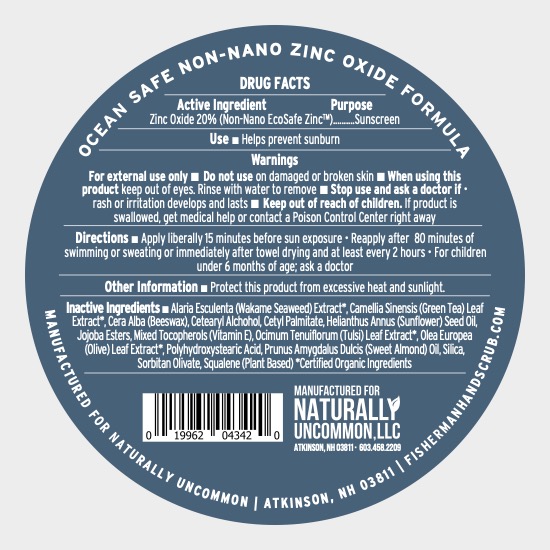 DRUG LABEL: Mackenzies SPF 40 Ocean Safe Sunscreen
NDC: 80325-040 | Form: CREAM
Manufacturer: Naturally Uncommon LLC
Category: otc | Type: HUMAN OTC DRUG LABEL
Date: 20240717

ACTIVE INGREDIENTS: ZINC OXIDE 20 g/100 g
INACTIVE INGREDIENTS: CETOSTEARYL ALCOHOL; CETYL PALMITATE; ALMOND OIL; SQUALENE; SUNFLOWER OIL; HOLY BASIL LEAF; POLYHYDROXYSTEARIC ACID (2300 MW); SILICON DIOXIDE; TOCOPHEROL; OLEA EUROPAEA LEAF; SORBITAN OLIVATE; ALARIA ESCULENTA; YELLOW WAX; JOJOBA OIL, RANDOMIZED; GREEN TEA LEAF

ACTIVE INGREDIENT

Zinc Oxide 20%

PURPOSE

Sunscreen.

INDICATIONS AND USAGE

Helps prevent sunscreen.

WARNINGS

- For external use only.
- Do not use on damaged or broken skin.
- When using this product, keep out of eyes. Rinse with water to remove.
- Stop use and ask a doctor if rash or irritation develops and lasts.

KEEP OUT OF REACH OF CHILDREN

If product is swallowed, get medical help or contact a Poison Control Center right away.

DOSAGE AND ADMINISTRATION

- Apply liberally 15 minutes before sun exposure.
- Reapply after 80 minutes of swimming or sweating or immediately after towel drying and at least every 2 hours.
- For children under 6 months of age; ask a doctor.

INACTIVE INGREDIENT

Alaria Esculenta (Wakame Seaweed) Extract*, Camellia Sinensis (Green Tea) Leaf Extract*, Cera Alba (Beeswax), Cetearyl Alcohol, Cetyl Palmitate, Helianthus Annus (Sunflower) Seed Oil, Jojoba Esters, Mixed Tocopherols (Vitamin E), Ocimum Tenuiflorum (Tulsi) Leaf Extract*, Olea Europea (Olive) Leaf Extract*, Polyhydroxystearic Acid, Prunus Amygdalus Dulcis (Sweet Almond) Oil, Silica, Sorbitan Olivate, Squalene (Plant Based)

*Certified Organic Ingredients